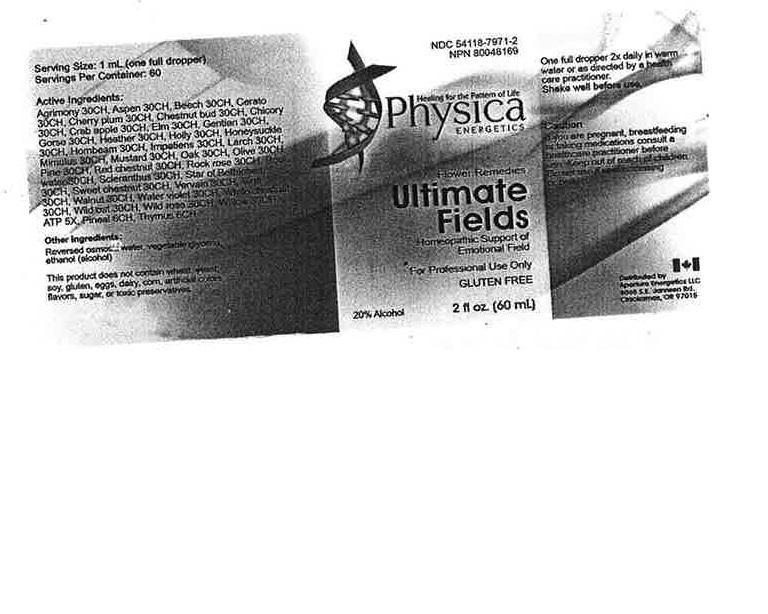 DRUG LABEL: Ultimate Fields
NDC: 54118-7971 | Form: SOLUTION/ DROPS
Manufacturer: ABCO Laboratories, Inc.
Category: homeopathic | Type: HUMAN OTC DRUG LABEL
Date: 20150715

ACTIVE INGREDIENTS: AGRIMONIA EUPATORIA 30 [hp_C]/60 mL; POPULUS ALBA WHOLE 30 [hp_C]/60 mL; FAGUS SYLVATICA FLOWERING TOP 30 [hp_C]/60 mL; CERATOSTIGMA WILLMOTTIANUM FLOWER 30 [hp_C]/60 mL; PRUNUS CERASIFERA FLOWER 30 [hp_C]/60 mL; AESCULUS HIPPOCASTANUM WHOLE 30 [hp_C]/60 mL; CICHORIUM INTYBUS FLOWER 30 [hp_C]/60 mL; MALUS SYLVESTRIS FLOWER 30 [hp_C]/60 mL; ULMUS ALATA WHOLE 30 [hp_C]/60 mL; GENTIANA ACAULIS 30 [hp_C]/60 mL; ULEX EUROPAEUS FLOWER 30 [hp_C]/60 mL; CALLUNA VULGARIS FLOWERING TOP 30 [hp_C]/60 mL; ILEX AQUIFOLIUM FLOWERING TOP 30 [hp_C]/60 mL; LONICERA CAPRIFOLIUM FLOWERING TOP 30 [hp_C]/60 mL; CARPINUS BETULUS FLOWERING TOP 30 [hp_C]/60 mL; IMPATIENS CAPENSIS WHOLE 30 [hp_C]/60 mL; LARIX DECIDUA WHOLE 30 [hp_C]/60 mL; MIMULUS GUTTATUS FLOWERING TOP 30 [hp_C]/60 mL; BRASSICA NIGRA WHOLE 30 [hp_C]/60 mL; QUERCUS ROBUR FLOWER 30 [hp_C]/60 mL; OLEA EUROPAEA FRUIT VOLATILE OIL 30 [hp_C]/60 mL; PINUS SYLVESTRIS FLOWERING TOP 30 [hp_C]/60 mL; AESCULUS CARNEA FLOWER 30 [hp_C]/60 mL; HELIANTHEMUM NUMMULARIUM FLOWER 30 [hp_C]/60 mL; SCLERANTHUS ANNUUS FLOWERING TOP 30 [hp_C]/60 mL; ORNITHOGALUM UMBELLATUM 30 [hp_C]/60 mL; CASTANEA SATIVA FLOWER 30 [hp_C]/60 mL; VERBENA OFFICINALIS FLOWERING TOP 30 [hp_C]/60 mL; VITIS VINIFERA FLOWERING TOP 30 [hp_C]/60 mL; JUGLANS REGIA FLOWERING TOP 30 [hp_C]/60 mL; HOTTONIA PALUSTRIS FLOWER 30 [hp_C]/60 mL; AESCULUS HIPPOCASTANUM FLOWER 30 [hp_C]/60 mL; AVENA FATUA WHOLE 30 [hp_C]/60 mL; ROSA CANINA FLOWER 30 [hp_C]/60 mL; SALIX ALBA FLOWERING TOP 30 [hp_C]/60 mL; ADENOSINE TRIPHOSPHATE 5 [hp_X]/60 mL; BOS TAURUS PINEAL GLAND 6 [hp_C]/60 mL; BOS TAURUS THYMUS 6 [hp_C]/60 mL
INACTIVE INGREDIENTS: WATER; ALCOHOL; GLYCERIN

Ultimate Fields

WARNINGS

- If you are pregnant, breastfeeding or taking medications consult a healthcare practitioner before use.
- Keep out of reach of children.
- Do not use if seal is missing or broken.

INACTIVE INGREDIENT

Reversed osmosis water, vegetable glycerin, ethanol (alcohol).

ACTIVE INGREDIENT

Agrimony 30C, Aspen 30C, Beech 30C, Cerato 30 C, Cherry Plum 30C, Chestnut Bud 30C, Chickory 30C, Crabapple 30C, Elm 30C, Gentian 30C, Gorse 30C, Heather 30C, Holly 30C, Honeysuckle 30C, Hornbeam 30C, Impatiens 30C, Larch 30C, Mimulus 30C, Mustard 30C, Oak 30C, Olive 30C, Pine 30C, Red Chestnut 30C, Rock Rose 30C, Rock Water 30C, Scleranthus 30C, Star of bethlehem 30C, Sweet Chestnut 30C, Vervain 30C, Vine 30C, Walnut 30C, Water Violet 30C, White Chestnut 30C, Wild Oats 30C, Wild Rose 30C, Willow 30C, ATP 5X, Pineal 6C, Thymus 6C.

KEEP OUT OF REACH OF CHILDREN!

DOSAGE AND ADMINISTRATION

- One full dropper 2x daily in warm water or as directed by a healthcare practitioner.
- Shake well before use.

PURPOSE

Homeopathic Support of Emotional Field

INDICATIONS AND USAGE

For Professional Use Only